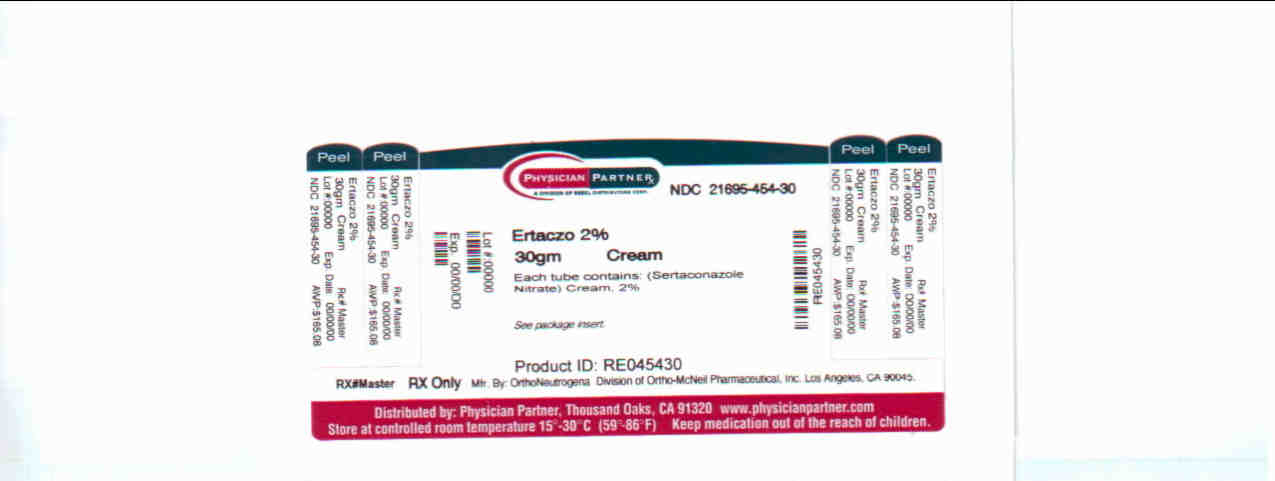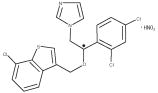 DRUG LABEL: ERTACZO
NDC: 21695-454 | Form: CREAM
Manufacturer: Rebel Distributors Corp.
Category: prescription | Type: HUMAN PRESCRIPTION DRUG LABEL
Date: 20090601

ACTIVE INGREDIENTS: Sertaconazole Nitrate 20 mg/1 g
INACTIVE INGREDIENTS: ETHYLENE GLYCOL; POLYETHYLENE GLYCOL; Light mineral oil; Methylparaben; Sorbic acid; Water

ERTACZO(sertaconazole nitrate) Cream, 2%

For Topical Dermatologic Use Only - Not for Oral, Ophthalmic or Intravaginal Use

DESCRIPTION

ERTACZO® (sertaconazole nitrate) Cream, 2%, contains the imidazole antifungal, sertaconazole nitrate. Sertaconazole nitrate contains one asymmetric carbon atom and exists as a racemic mixture of equal amounts of R and S enantiomers.

Sertaconazole nitrate is designated chemically as (±)-1-[2,4-dichloro-β-[(7-chlorobenzo-[b]thien-3-yl)methoxy]phenethyl]imidazole nitrate. It has a molecular weight of 500.8. The molecular formula is C20H15Cl3N2OS • HNO3, and the structural formula is as follows:

Sertaconazole nitrate is a white or almost white powder. It is practically insoluble in water, soluble in methanol, sparingly soluble in alcohol and in methylene chloride. Each gram of ERTACZO® Cream, 2%, contains 17.5 mg of sertaconazole (as sertaconazole nitrate, 20 mg) in a white cream base of ethylene glycol and polyethylene glycol palmitostearate, glyceryl isostearate, light mineral oil, methylparaben, polyoxyethylened saturated glycerides and glycolized saturated glycerides, sorbic acid and purified water.

CLINICAL PHARMACOLOGY

Pharmacokinetics: In a multiple dose pharmacokinetic study that included 5 male patients with interdigital tinea pedis (range of diseased area, 42 - 140 cm^2; mean, 93 cm^2), ERTACZO® Cream, 2%, was topically applied every 12 hours for a total of 13 doses to the diseased skin (0.5 grams sertaconazole nitrate per 100 cm^2). Sertaconazole concentrations in plasma measured by serial blood sampling for 72 hours after the thirteenth dose were below the limit of quantitation (2.5 ng/mL) of the analytical method used.

Microbiology: Sertaconazole is an antifungal that belongs to the imidazole class of antifungals. While the exact mechanism of action of this class of antifungals is not known, it is believed that they act primarily by inhibiting the cytochrome P450-dependent synthesis of ergosterol. Ergosterol is a key component of the cell membrane of fungi, and lack of this component leads to fungal cell injury primarily by leakage of key constituents in the cytoplasm from the cell.

Activity In Vivo: Sertaconazole nitrate has been shown to be active against isolates of the following microorganisms in clinical infections as described in the INDICATIONS AND USAGE section:

Trichophyton rubrum

Trichophyton mentagrophytes

Epidermophyton floccosum

CLINICAL STUDIES

In two randomized, double-blind, clinical trials, patients 12 years and older with interdigital tinea pedis applied either ERTACZO® Cream, 2%, or vehicle, twice daily for four weeks. Patients with moccasin-type (plantar) tinea pedis and/or onychomycosis were excluded from the study. Two weeks after completion of therapy (six weeks after beginning therapy), patients were evaluated for signs and symptoms related to interdigital tinea pedis.

Treatment outcomes are summarized in the table below.

Treatment Outcomes as Percent (%) of Total Subjects
 | Study 1 |  | Study 2
 | Sertaconazole | Vehicle | Sertaconazole | Vehicle
Complete Cure* (Primary Efficacy Variable) | 13/99 (13.1%) | 3/92 (3.3%) | 28/103 (27.2%) | 5/103 (4.9%)
Effective Treatment** | 32/99 (32.3%) | 11/92 (12.0%) | 52/103 (50.5%) | 16/103 (15.5%)
Mycological Cure*** | 49/99 (49.5%) | 18/92 (19.6%) | 71/103 (68.9%) | 20/103 (19.4%)
* Complete Cure - Patients who had complete clearing of signs and symptoms and Mycological Cure.
** Effective Treatment - Patients who had minimal residual signs and symptoms of interdigital tinea pedis and Mycological Cure.
*** Mycological Cure - Patients who had both negative microscopic KOH preparation and a negative fungal culture.

In clinical trials, complete cure in sertaconazole treated patients was achieved in 32 of 160 (20%) patients with Trichophyton rubrum, in 7 of 28 (25%) patients with Trichophyton mentagrophytes and in 2 of 13 (15%) patients with Epidermophyton floccosum.

INDICATIONS AND USAGE

ERTACZO® (sertaconazole nitrate) Cream, 2%, is indicated for the topical treatment of interdigital tinea pedis in immunocompetent patients 12 years of age and older, caused by: Trichophyton rubrum, Trichophyton mentagrophytes, and Epidermophyton floccosum (see CLINICAL STUDIES Section).

CONTRAINDICATIONS

ERTACZO® Cream, 2%, is contraindicated in patients who have a known or suspected sensitivity to sertaconazole nitrate or any of its components or to other imidazoles.

WARNINGS

ERTACZO® Cream, 2%, is not indicated for ophthalmic, oral or intravaginal use.

PRECAUTIONS

GENERAL PRECAUTIONS

General: ERTACZO® Cream, 2%, is for use on the skin only. If irritation or sensitivity develops with the use of ERTACZO® Cream, 2%, treatment should be discontinued and appropriate therapy instituted.

Diagnosis of the disease should be confirmed either by direct microscopic examination of infected superficial epidermal tissue in a solution of potassium hydroxide or by culture on an appropriate medium.

Physicians should exercise caution when prescribing ERTACZO® Cream, 2%, to patients known to be sensitive to imidazole antifungals, since cross-reactivity may occur.

PATIENT COUNSELING INFORMATION

Information for Patients: The patient should be instructed to:

1. Use ERTACZO® Cream, 2%, as directed by the physician. The hands should be washed after applying the medication to the affected area(s). Avoid contact with the eyes, nose, mouth and other mucous membranes. ERTACZO® Cream, 2%, is for external use only.
2. Dry the affected area(s) thoroughly before application, if you wish to use ERTACZO® Cream, 2%, after bathing.
3. Use the medication for the full treatment time recommended by the physician, even though symptoms may have improved. Notify the physician if there is no improvement after the end of the prescribed treatment period, or sooner, if the condition worsens.
4. Inform the physician if the area of application shows signs of increased irritation, redness, itching, burning, blistering, swelling or oozing.
5. Avoid the use of occlusive dressings unless otherwise directed by the physician.
6. Do not use this medication for any disorder other than that for which it was prescribed.

DRUG AND OR LABORATORY TEST INTERACTIONS

Drug/Laboratory Test Interactions: Potential interactions between ERTACZO® Cream, 2%, and other drugs or laboratory tests have not been systematically evaluated.

CARCINOGENESIS AND MUTAGENESIS AND IMPAIRMENT OF FERTILITY

Carcinogenesis, Mutagenesis, Impairment of Fertility: Long-term studies to evaluate the carcinogenic potential of sertaconazole nitrate have not been conducted. No clastogenic potential was observed in a mouse micronucleus test. Sertaconazole nitrate was considered negative for sister chromatid exchange (SCE) in the in vivo mouse bone marrow SCE assay. There was no evidence that sertaconazole nitrate induced unscheduled DNA synthesis in rat primary hepatocyte cultures. Sertaconazole nitrate exhibited no toxicity or adverse effects on reproductive performance or fertility of male or female rats given up to 60 mg/kg/day orally by gastric intubation (16 times the maximum recommended human dose based on a body surface area comparison).

PREGNANCY

Pregnancy: Teratogenic Effects. Pregnancy Category C: Oral reproduction studies in rats and rabbits did not produce any evidence of maternal toxicity, embryotoxicity or teratogenicity of sertaconazole nitrate at an oral dose of 160 mg/kg/day (40 times (rats) and 80 times (rabbits) the maximum recommended human dose on a body surface area comparison). In an oral peri-postnatal study in rats, a reduction in live birth indices and an increase in the number of still-born pups was seen at 80 and 160 mg/kg/day.

There are no adequate and well-controlled studies that have been conducted on topically applied ERTACZO® Cream, 2%, in pregnant women. Because animal reproduction studies are not always predictive of human response, ERTACZO® Cream, 2%, should be used during pregnancy only if clearly needed.

NURSING MOTHERS

Nursing Mothers: It is not known if sertaconazole is excreted in human milk. Because many drugs are excreted in human milk, caution should be exercised when prescribing ERTACZO® Cream, 2%, to a nursing woman.

PEDIATRIC USE

Pediatric Use: The efficacy and safety of ERTACZO® Cream, 2%, have not been established in pediatric patients below the age of 12 years.

GERIATRIC USE

Geriatric Use: Clinical studies of ERTACZO® Cream, 2%, did not include sufficient numbers of subjects aged 65 and over to determine whether they respond differently from younger subjects.

ADVERSE EVENTS

In clinical trials, cutaneous adverse events occurred in 7 of 297 (2%) patients (2 of them severe) receiving ERTACZO® Cream, 2%, and in 7 of 291 (2%) patients (2 of them severe) receiving vehicle. These reported cutaneous adverse events included contact dermatitis, dry skin, burning skin, application site reaction and skin tenderness.

In a dermal sensitization study, 8 of 202 evaluable patients tested with ERTACZO® Cream, 2%, and 4 of 202 evaluable patients tested with vehicle, exhibited a slight erythematous reaction in the challenge phase. There was no evidence of cumulative irritation or contact sensitization in a repeated insult patch test involving 202 healthy volunteers. In non-US post-marketing surveillance for ERTACZO® Cream, 2%, the following cutaneous adverse events were reported: contact dermatitis, erythema, pruritus, vesiculation, desquamation, and hyperpigmentation.

OVERDOSAGE

Overdosage with ERTACZO® Cream, 2%, has not been reported to date. ERTACZO® Cream, 2%, is intended for topical dermatologic use only. It is not for oral, ophthalmic, or intravaginal use.

DOSAGE AND ADMINISTRATION

In the treatment of interdigital tinea pedis, ERTACZO® Cream, 2%, should be applied twice daily for 4 weeks. Sufficient ERTACZO® Cream, 2%, should be applied to cover both the affected areas between the toes and the immediately surrounding healthy skin of patients with interdigital tinea pedis. If a patient shows no clinical improvement 2 weeks after the treatment period, the diagnosis should be reviewed.

HOW SUPPLIED

ERTACZO® Cream, 2%, is supplied in tubes in the following size:

30-gram tube NDC 21695-454-30

Store at 25°C (77°F); excursions permitted to 15º-30°C (59º-86°F) [see USP Controlled Room Temperature].

Rx only.

Patent No. 5,135,943

Distributed By: OrthoNeutrogena
DIVISION OF ORTHO-McNEIL PHARMACEUTICAL, INC.
Los Angeles, CA 90045

Repackaged By: Rebel Distributors
Thousand Oaks, CA 91320

Rev November 2005
128354